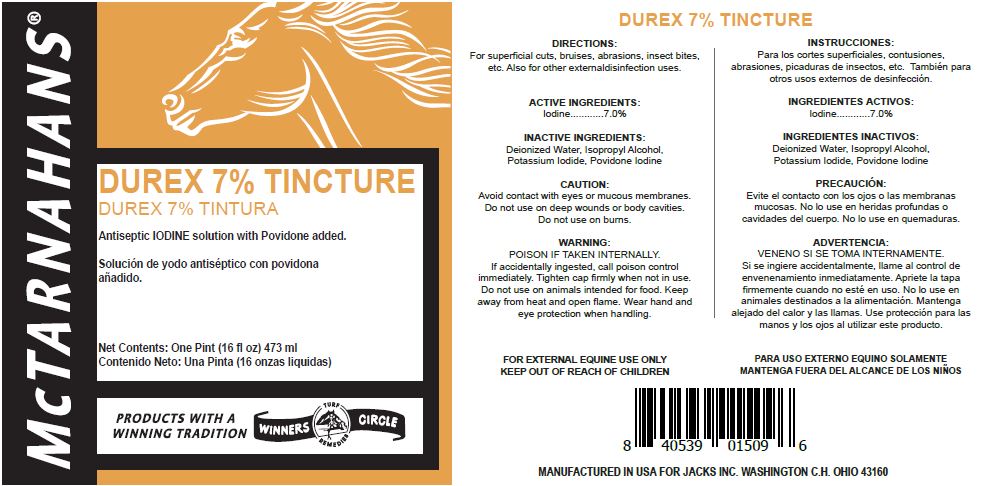 DRUG LABEL: Durex 7% Tincture Iodine
NDC: 61156-109 | Form: LINIMENT
Manufacturer: JACKS MFG INC
Category: animal | Type: OTC ANIMAL DRUG LABEL
Date: 20211208

ACTIVE INGREDIENTS: IODINE 0.33 g/1 mL
INACTIVE INGREDIENTS: POTASSIUM IODIDE 0.22 g/1 mL; ISOPROPYL ALCOHOL 3.67 mL/1 mL; WATER 0.94 mL/1 mL; POVIDONE-IODINE 0.03 g/1 mL

DUREX 7% TINCTURE

DIRECTIONS

For superficial cuts, bruises, abrasions, insect bites, etc.

Also for other external disinfection uses.

CAUTION

Avoid contact with eyes or mucous membranes.
Do not use on deep wounds or body cavities.
Do not use on burns.

WARNING POISON IF TAKEN INTERNALLY.

If accidentally ingested, call poison control immediately. Tighten cap firmly when not in use.

Do not use on animals intended for food.

Keep away from heat and open flame.

Wear hand and eye protection when handling.